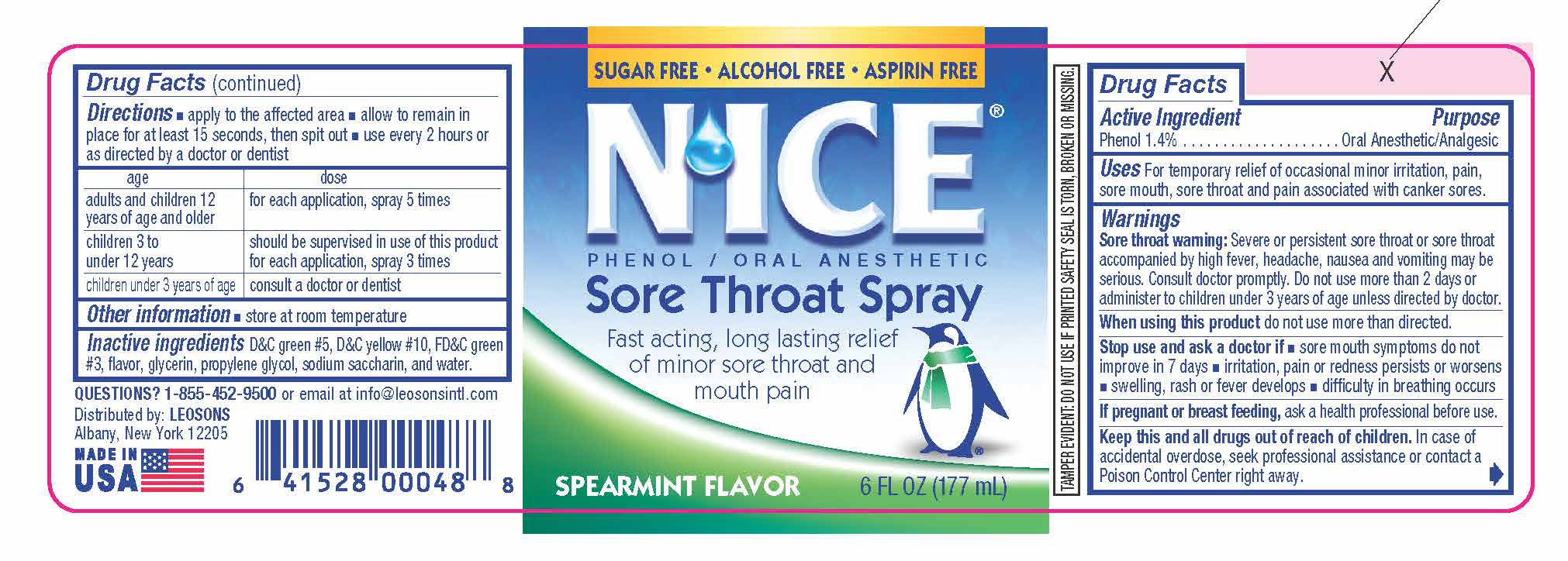 DRUG LABEL: NICE SORE THROAT Spearmint
NDC: 69626-0048 | Form: SPRAY
Manufacturer: Leosons Overseas Corp
Category: otc | Type: HUMAN OTC DRUG LABEL
Date: 20241120

ACTIVE INGREDIENTS: PHENOL 1.4 g/177 mL
INACTIVE INGREDIENTS: PROPYLENE GLYCOL; GLYCERIN; D&C GREEN NO. 5; WATER; SACCHARIN SODIUM; FD&C GREEN NO. 3; D&C YELLOW NO. 10

NICE Sore Throat Spearmint

Active Ingredient & Purposes

PURPOSE

Active Ingredients | Purposes
Phenol 1.4% | Oral Anesthetic/ Analgesic

Uses

For temporary relief of occasional minor irritation, pain, sore mouth, sore throat and pain associated with canker sores.

Warnings

Sore throat warning: Severe or persistent sore throat or sore throat accompanied by high fever, headache, nausea and vomiting may be serious. Consult doctor promptly. Do not use more than 2 days or administer to children under 3 years of age unless directed by doctor.

When using this product

- do not use more than directed.

Stop use and ask a doctor if

- sore mouth symptoms do not improve in 7 days
- irritation, pain or redness persists or worsens
- swelling, rash or fever develops
- difficulty in breathing occurs

If pregnant or breast feeding,

ask a health professional before use.

Keep this and all drugs out of reach of children.

In case of accidental overdose, seek professional assistance or contact a Poison Control Center right away.

Directions

- apply to the affected area
- allow to remain in place for at least 15 seconds, then spit out
- use every 2 hours or as directed by a doctor or dentist

age | dose
adults and children 12 years of age and older | for each application, spray 5 times
children 3 to under 12 years | should be supervised in use of this product; for each application, spray 3 times
children under 3 years of age | consult a doctor or dentist

Other Information

- store at room temperature

TAMPER EVIDENT: DO NOT USE IF PRINTED SAFETY SEAL IS TORN, BROKEN OR MISSING.

Inactive Ingredients

D&C green #5, D&C yellow #10, FD&C green #3, flavor, glycerin, propylene glycol, sodium saccharin, and water.

Questions?

1-855-452-9500 or email at info@leosonsintl.com

Distributed by:

LEOSONS
Albany, New York 12205

Made in USA

Principal Display Panel

SUGAR FREE • ALCOHOL FREE • ASPIRIN FREE

N'ICE®

P H E N O L / O R A L A N E S T H E T I C

Sore Throat Spray

Fast acting, long lasting relief of minor sore throat and mouth pain

SPEARMINT FLAVOR

6 FL OZ (177 mL)